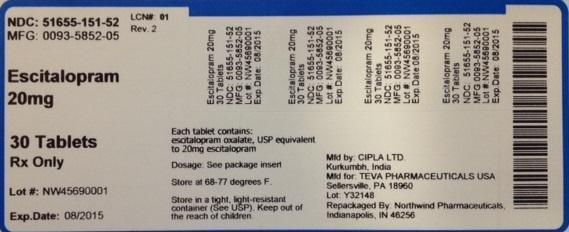 DRUG LABEL: Escitalopram
NDC: 51655-151 | Form: TABLET, FILM COATED
Manufacturer: Northwind Pharmaceuticals
Category: prescription | Type: HUMAN PRESCRIPTION DRUG LABEL
Date: 20140606

ACTIVE INGREDIENTS: ESCITALOPRAM OXALATE 20 mg/1 1

Label display

NDC: 51655-151-52

MFG: 0093-5852-05

Escitalopram 20 mg

30 tablets

Rx only

Lot#:

Exp. Date:

Each tablet contains: escitalopram oxalate, USP equivalent to 20 mg escitalopram

Dosage: See package insert

Store at 6877 degrees F.

Store in a tight, light-resistant container (See USP). Keep out of the reach of children.

Mfg by: Cipla Ltd, Kurkumbh, India

Mfg for: Teva Pharmaceuticals USA, Sellersville, PA 18960 Lot#:

Repackaged by Northwind Pharmaceuticals, Indianapolis, IN 46256

Indications and usage

Escitalopram is a selective serotonin reuptake inhibitor (SSRI) indicated for:

Acute and Maintenance Treatment of Major Depressive Disorder (MDD) in adults and adolescents aged 12 to 17 years

Acute Treatment of Generalized Anxiety Disorder (GAD) in adults

Contraindications

Serotonin Syndrome and MAOIs: Do not use MAOIs intended to treat psychiatric disorders with escitalopram or within 14 days of stopping treatment with escitalopram.

Do not use escitalopram within 14 days of stopping an MAOI intended to treat psychiatric disorders. In addition, do not start escitalopram in a patient who is being treated with linezolid or intravenous methylene blue.

Pimozide: Do not use concomitantly.

Known hypersensitivity to escitalopram or citalopram or any of the inactive ingredients

Warnings and Precautions

Clinical Worsening/Suicide Risk: Monitor for clinical worsening, suicidality and unusual change in behavior, especially during the initial few months of therapy or at times of dose changes .

Serotonin Syndrome: Serotonin syndrome has been reported with SSRIs and SNRIs, including escitalopram, both when taken alone, but especially when coadministered with other serotonergic agents (including triptans, tricyclic antidepressants, fentanyl, lithium, tramadol, tryptophan, buspirone and St. John’s Wort). If such symptoms occur, discontinue escitalopram and initiate supportive treatment. If concomitant use of escitalopram with other serotonergic drugs is clinically warranted, patients should be made aware of a potential increased risk for serotonin syndrome, particularly during treatment initiation and dose increases.

Discontinuation of Treatment with Escitalopram: A gradual reduction in dose rather than abrupt cessation is recommended whenever possible.

Seizures: Prescribe with care in patients with a history of seizure.

Activation of Mania/Hypomania: Use cautiously in patients with a history of mania.

Hyponatremia: Can occur in association with SIADH (5.6).Abnormal Bleeding: Use caution in concomitant use with NSAIDs, aspirin, warfarin or other drugs that affect coagulation.

Interference with Cognitive and Motor Performance: Use caution when operating machinery.

Use in Patients with Concomitant Illness: Use caution in patients with diseases or conditions that produce altered metabolism or hemodynamic responses